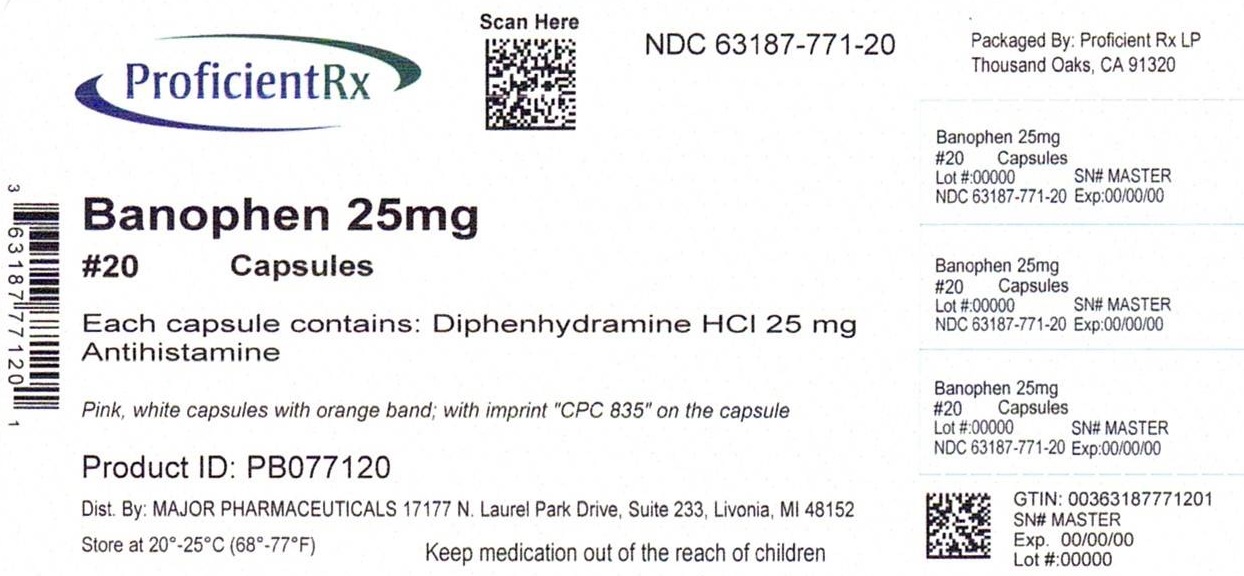 DRUG LABEL: Diphenhydramine Hydrochloride
NDC: 63187-771 | Form: CAPSULE
Manufacturer: Proficient Rx LP
Category: otc | Type: HUMAN OTC DRUG LABEL
Date: 20240101

ACTIVE INGREDIENTS: DIPHENHYDRAMINE HYDROCHLORIDE 25 mg/1 1
INACTIVE INGREDIENTS: LACTOSE, UNSPECIFIED FORM; STARCH, CORN; GELATIN, UNSPECIFIED; SILICON DIOXIDE; CROSCARMELLOSE SODIUM; FD&C BLUE NO. 1; FD&C RED NO. 40; MAGNESIUM STEARATE; D&C RED NO. 28

Diphenhydramine Hydrochloride Capsules

Active ingredient

Diphenhydramine Hydrochloride 25 mg

Purpose

Antihistamine

Use

Temporarily relieves these symptoms due to hay fever or other upper respiratory allergies and common cold, sneezing, runny nose, itchy, watery eyes, itchy throat and nose.

Warnings: Do not use

• to make a child sleepy

• with any other product containing diphenhydramine, even one used on skin

Ask a doctor before use if you have

• a breathing problem such as emphysema or chronic bronchitis

• glaucoma

• trouble urinating due to an enlarged prostate gland

When using this product

• marked drowsiness may occur

• avoid alcoholic drinks

• alcohol, sedatives, and tranquilizers may increase drowsiness

• be careful when driving a motor vehicle or operating machinery

• excitability may occur, especially in children

Pregnancy/breast-feeding warning

If pregnant or breast-feeding, ask a health professional before use.

Keep out of reach of children. In case of overdose, get medical help or contact a Poison Control Center right away.

Directions

Adults and children 12 years and over: take 25 to 50 mg (1 to 2 capsule) every 4 to 6 hours, not more than 12 capsules in 24 hours.

Children 6 years to 12 years of age: take 12.5 mg** (1 capsule) every 4 to 6 hours, not more than 6 capsules in 24 hours.

Children under 6 years of age: do not use

**12.5mg dosage strength is not available in this package. Do not attempt to break capsule

Other information

Store at 20º-25ºC (68º-77ºF); excursions permitted to 15º-30ºC (59º-86ºF). [See USP Controlled Room Temperature]. Protect from excessive moisture.

Inactive ingredients

D&C Red #28, FD&C Blue #1, FD&C Red #40, Gelatin, Lactose and Starch.

Questions?

Questions or comments? (800) 616-2471

Distributed by

MAJOR® PHARMACEUTICALS

31778 Enterprise Drive

Livonia, MI 48150 USA

Repackaged by:

Proficient Rx LP

Thousand Oaks, CA 91320

Re-Order No. 301574